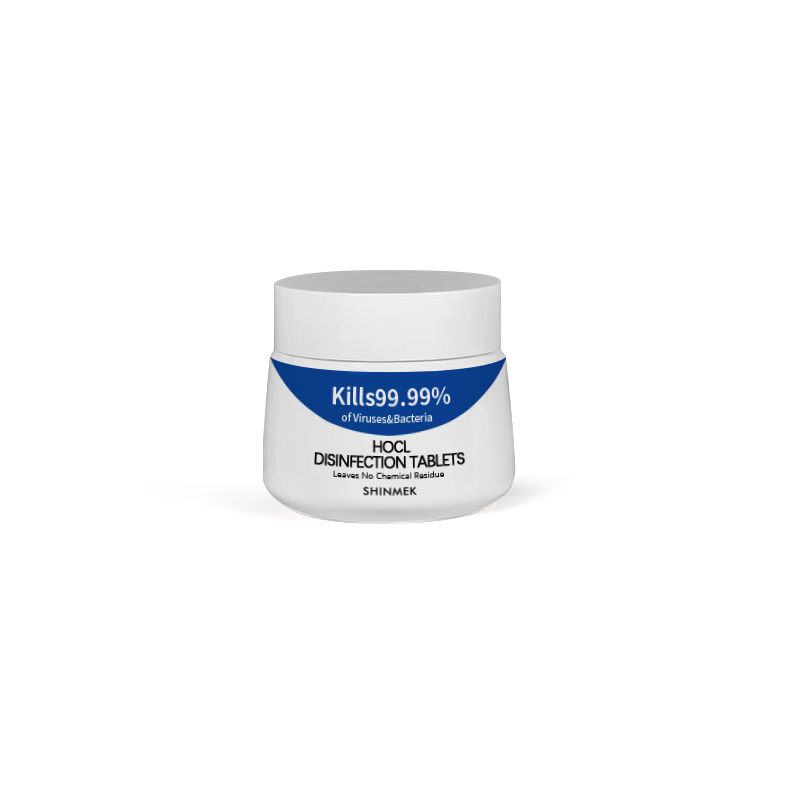 DRUG LABEL: Disinfection-Tablets
NDC: 82377-301 | Form: SOLUTION
Manufacturer: Jinhua Shuxin Pharmaceutical Biotechnology Co., Ltd.
Category: otc | Type: HUMAN OTC DRUG LABEL
Date: 20230131

ACTIVE INGREDIENTS: HYPOCHLOROUS ACID 0.8 mg/1 mg
INACTIVE INGREDIENTS: SODIUM CHLORIDE

消毒片

Disinfection Tablets

Active Ingredient(s)

HOCL 80% w/w. Purpose: Antiseptic

Purpose

Antiseptic, Disinfection Tablets

Use

Disinfection Tablets to help reduce bacteria that potentially can cause disease.

Warnings

For external use only.

Do not use

- in children less than 2 months of age
- on open skin wounds

When using this product keep out of eyes, ears, and mouth. In case of contact with eyes, rinse eyes thoroughly with water.
Stop use and ask a doctor if irritation or rash occurs. These may be signs of a serious condition.
Keep out of reach of children. If swallowed, get medical help or contact a Poison Control Center right away.

Stop use and ask a doctor if irritation or rash occurs. These may be signs of a serious condition.

Keep out of reach of children. If swallowed, get medical help or contact a Poison Control Center right away.

Directions

- Simply drop 1 tablet into 17 fl oz(500mL) of clean water. Let the tablet dissolve to form the sterilising solution. Spray on the skin 3-5 times each use. No rinsing reqiured.

Other information

- Store between 15-30C (59-86F)

Inactive ingredients

SODIUM CHLORIDE